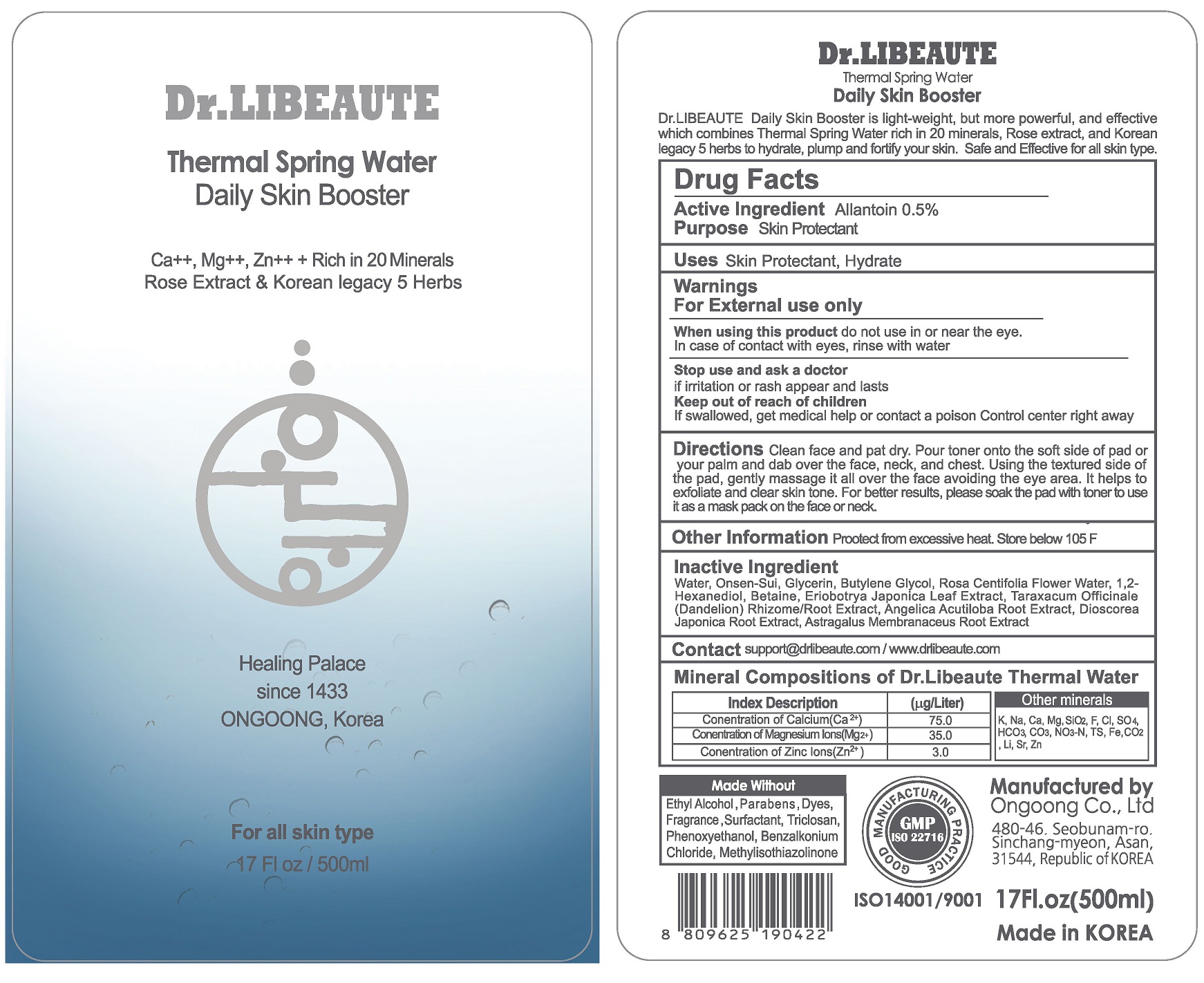 DRUG LABEL: Dr.LIBEAUTE Thermal Spring Water
NDC: 74084-0011 | Form: LIQUID
Manufacturer: Ongoong Co Ltd
Category: otc | Type: HUMAN OTC DRUG LABEL
Date: 20210130

ACTIVE INGREDIENTS: ALLANTOIN 0.5 g/100 mL
INACTIVE INGREDIENTS: GLYCERIN; BUTYLENE GLYCOL; WATER

Drug Facts

ACTIVE INGREDIENT

allantoin

INACTIVE INGREDIENT

water, glycerin, butylene glycol, etc.

PURPOSE

skin protecttant, hydrate

KEEP OUT OF REACH OF THE CHILDREN

INDICATIONS AND USAGE

clean face and pat dry.

pour toner onto the soft side onf pad or your palm and dab over the face, neck, and chest

(please refer to the directions on the label)

WARNINGS

For external use only.

When using this product keep out of eyes. If contact with eyes occurs, rinse promptly and thoroughly with water.

Stop use and ask a doctor if significant irritation or sensitization develops.

Keep out of reach of children. If swallowed, get medical help or contact a Poison Control Center right away.

DOSAGE AND ADMINISTRATION

for external use only